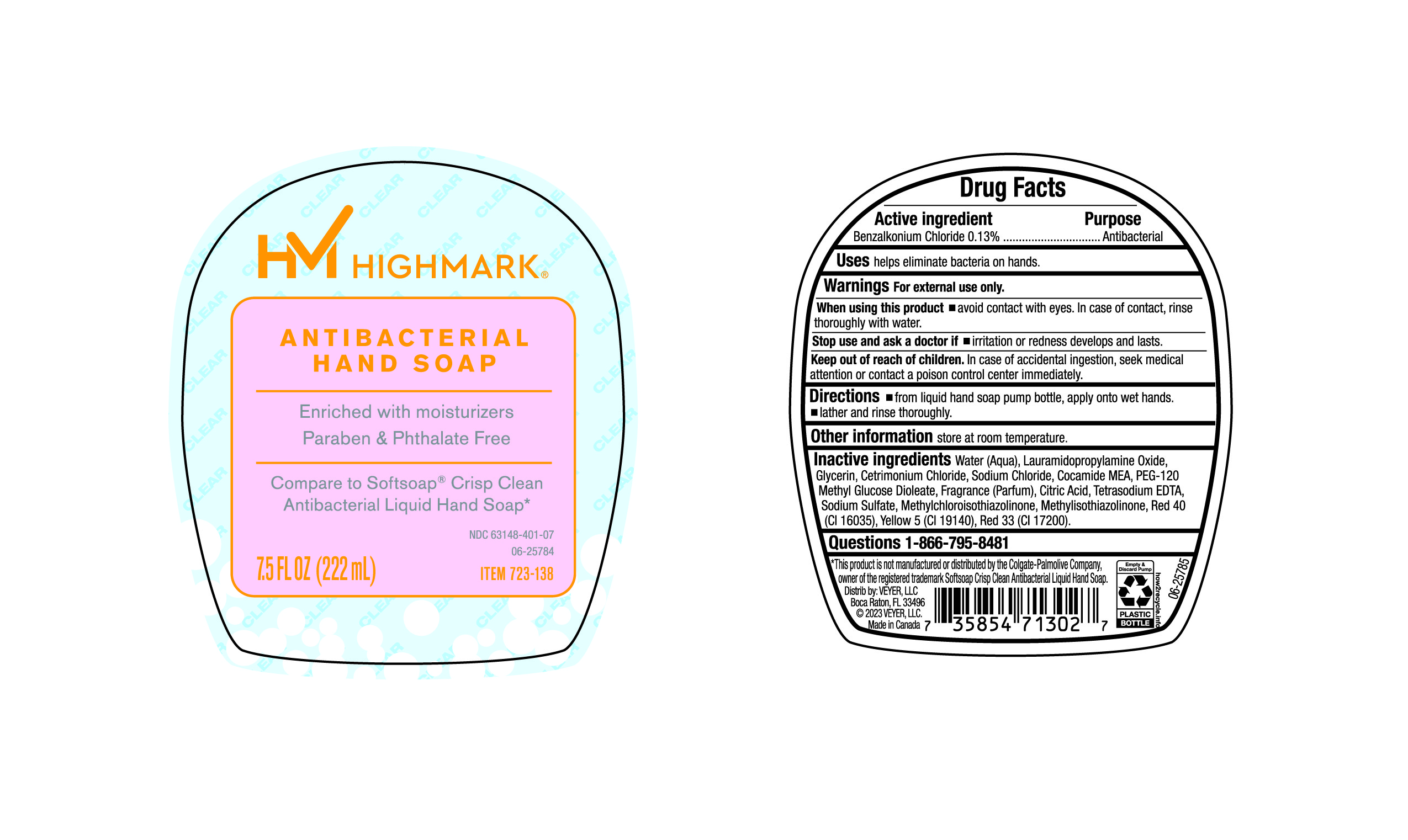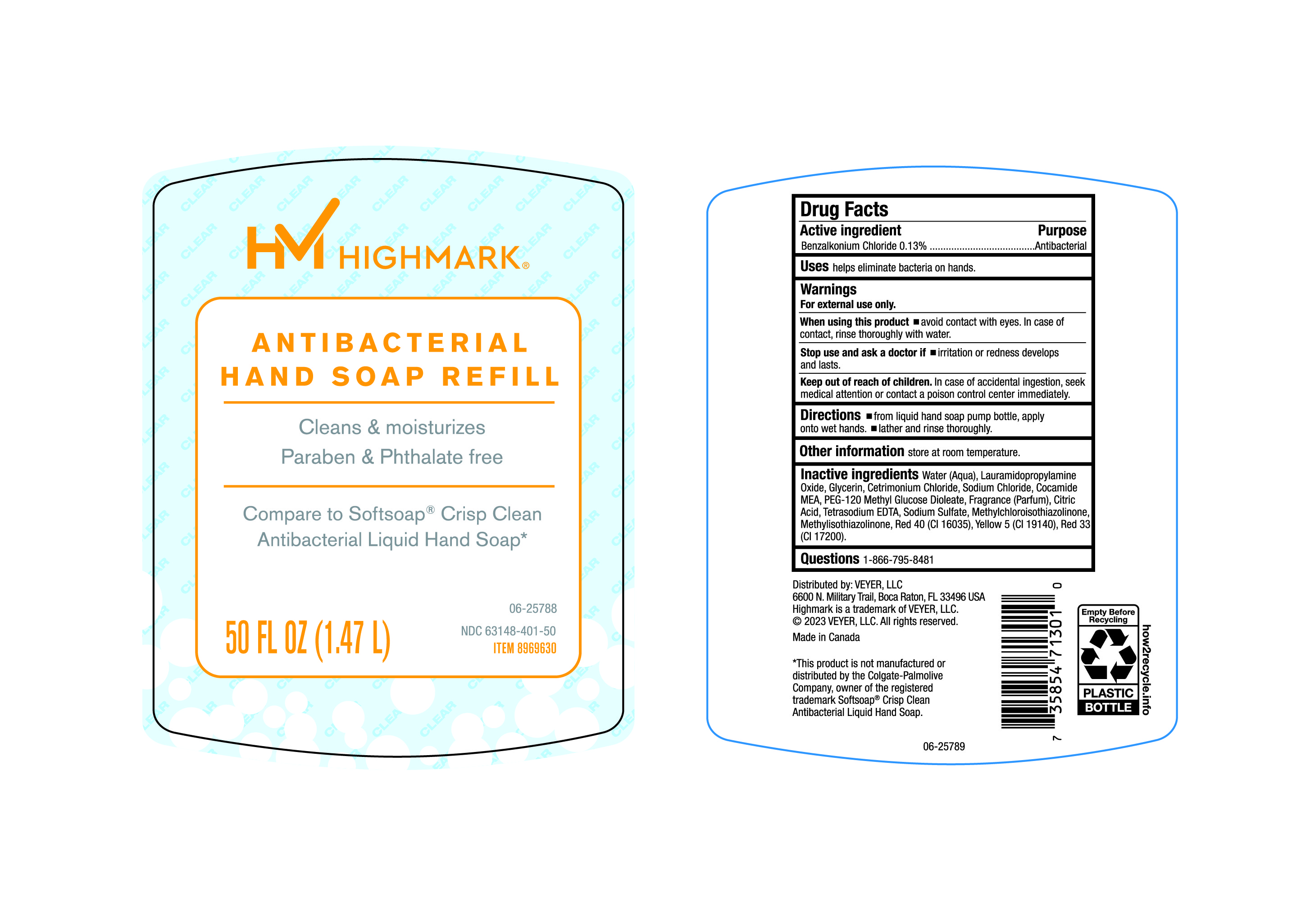 DRUG LABEL: HIMark
NDC: 63148-401 | Form: LIQUID
Manufacturer: Apollo Health and Beauty Care
Category: otc | Type: HUMAN OTC DRUG LABEL
Date: 20250206

ACTIVE INGREDIENTS: BENZALKONIUM CHLORIDE 130 mg/100 mL
INACTIVE INGREDIENTS: WATER; SODIUM CHLORIDE; COCO MONOETHANOLAMIDE; FRAGRANCE CLEAN ORC0600327; METHYLCHLOROISOTHIAZOLINONE; FD&C RED NO. 40; BASIC YELLOW 5; GLYCERIN; PEG-120 METHYL GLUCOSE DIOLEATE; METHYLISOTHIAZOLINONE; D&C RED NO. 33; LAURAMIDOPROPYLAMINE OXIDE; CETRIMONIUM CHLORIDE; EDETATE SODIUM; SODIUM SULFATE; ANHYDROUS CITRIC ACID

63148-401, HiMark Antibacterial Hand soap Refill.

Active Ingredient

Benzalkonium Chloride 0.13%

Purpose

Antibacterial

Uses

Helps eliminate bacteria on hands

Warnings

For External Use only

When using this product

- Avoid contact with eyes. In case of contact, rinse thoroughly with water.

Stop use and ask a doctor if

- irritation or redness develops and lasts.

Keep out of reach of children.

In case of accidental ingestion, seek medical attention or contact a poison control center immediately.

Directions

- From Liquid Hand Soap pump bottle, apply onto wet hands
- Lather and rinse thoroughly.

Other Information

Store at room Temperature.

Inactive Ingredients

Water (Aqua), Lauramidopropylamine Oxide, Glycerin, Cetrimonium Chloride, Sodium Chloride, Cocamide MEA, PEG-120 Methyl Glucose Dioleate, Fragrance (Parfum), Citric Acid, Tetrasodium EDTA, Sodium Sulfate, Methylchloroisothiazolinone, Methylisothiazolinone, Red 40 (CI 16035), Yellow 5(CI19140), Red 33 (CI17200).

Questions

1-866-795-8481